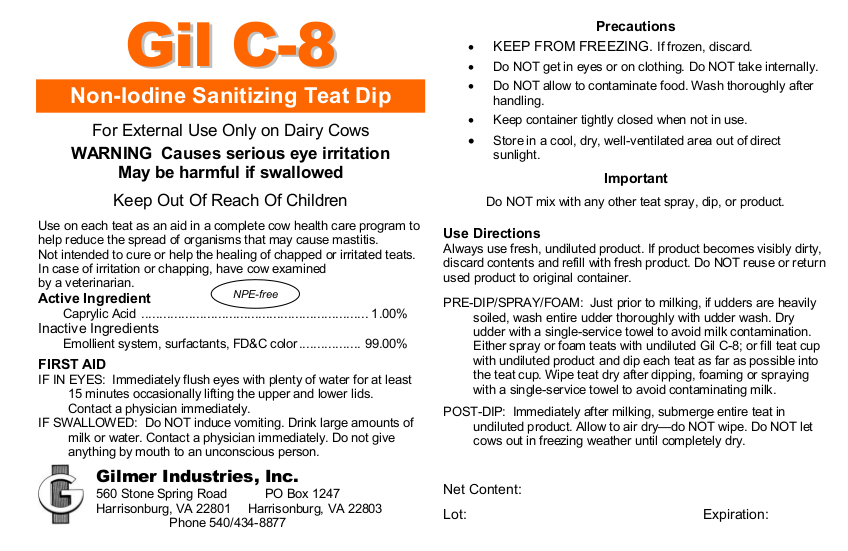 DRUG LABEL: Gil C-8
NDC: 54420-019 | Form: LIQUID
Manufacturer: Gilmer Industries, Inc.
Category: animal | Type: OTC ANIMAL DRUG LABEL
Date: 20210129

ACTIVE INGREDIENTS: CAPRYLIC/CAPRIC ACID 10000 mg/1 L

Gil C-8

PURPOSE

Non-Iodine Sanitizing Teat Dip

Use on each teat as an aid in a complete cow health care program to help reduce the spread of organisms that may cause mastitis.
Not intended to cure or help the healing of chapped or irritated teats.
In case of irritation or chapping, have cow examined by a veterinarian.

ACTIVE INGREDIENT

Caprylic Acid............................................ 1.00%

INACTIVE INGREDIENTS

Emollients, surfactants, FD&C color ..... 99.00%

USER SAFETY WARNINGS

For External Use Only on Dairy Cows

WARNING
Causes serious eye irritation
May be harmful if swallowed

Keep Out Of Reach Of Children

PRECAUTIONS

- KEEP FROM FREEZING. If frozen, discard.
- Do NOT get in eyes or on clothing.
- Do NOT take internally.
- Do NOT allow to contaminate food.
- Wash thoroughly after handling.
- Keep container tightly closed when not in use.
- Store in a cool, dry, well-ventilated area out of direct sunlight.

FIRST AID

IF IN EYES: Immediately flush eyes with plenty of water for at least
15 minutes occasionally lifting the upper and lower lids.
Contact a physician immediately.

IF SWALLOWED: Do NOT induce vomiting.
Drink large amounts of milk or water.
Contact a physician immediately.
Do not give anything by mouth to an unconscious person.

DIRECTIONS

Important: Do NOT mix with other teat spray, dip or product.

Always use fresh, undiluted product. If product becomes visibly dirty, discard contents and refill with fresh product.
Do NOT reuse or return used product to original container.

PRE-DIP/SPRAY/FOAM: Just prior to milking, if udders are heavily soiled, wash entire udder thoroughly with udder wash.
Dry udder with a single-service towel to avoid milk contamination.
Either spray or foam teats with undiluted Gil C-8; or fill teat cup with undiluted product and dip each teat as far as possible into the teat cup.
Wipe teat dry after dipping, foaming or spraying with a single-service towel to avoid contaminating milk.

POST-DIP: Immediately after milking, submerge entire teat in undiluted product.
Allow to air dry—do NOT wipe.
Do NOT let cows out in freezing weather until completely dry.